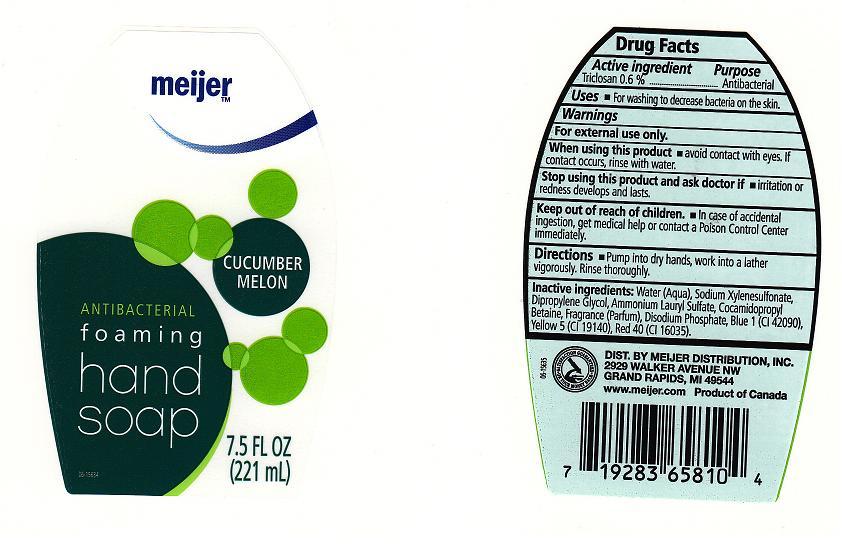 DRUG LABEL: MEIJER
NDC: 41250-167 | Form: SOAP
Manufacturer: MEIJER
Category: otc | Type: HUMAN OTC DRUG LABEL
Date: 20101008

ACTIVE INGREDIENTS: TRICLOSAN 0.6 mL/100 mL
INACTIVE INGREDIENTS: WATER; SODIUM POLYSTYRENE SULFONATE; DIPROPYLENE GLYCOL; AMMONIUM LAURYL SULFATE; COCAMIDOPROPYL BETAINE; SODIUM PHOSPHATE, DIBASIC, DIHYDRATE; FD&C BLUE NO. 1; FD&C YELLOW NO. 5; FD&C RED NO. 4

ACTIVE INGREDIENT

TRICLOSAN (0.6%)

PURPOSE

ANTIBACTERIAL

USES

FOR WASHING TO DECREASE BACTERIA ON THE SKIN

DIRECTIONS

PUMP INTO DRY HANDS. WORK INTO LATHER VIGOROUSLY. RINSE THOROUGHLY.

WARNINGS

FOR EXTERNAL USE ONLY

WHEN USING THIS PRODUCT

AVOID CONTACT WITH EYES. IF CONTACT OCCURS RINSE WITH WATER.

STOP USING THE PRODUCT AND ASK DOCTOR IF

IRRITATION OR REDNESS DEVELOPS AND LASTS.

KEEP OUT OF REACH OF CHILDREN

IN CASE OF ACCIDENTAL INGESTION GET MEDICAL HELP OR CONTACT POISON CONTROL CENTER IMMEDIATELY.

INACTIVE INGREDIENTS

Water (Aqua), Sodium Xylenesulfonate, Dipropylene Glycol, Ammonium Lauryl Sulfate, Cocamidopropyl Betaine, Fragrance(Parfum), Disodium Phosphate, Citric Acid, Blue 1 (CI 42090), Yellow 5 (CI 19140), Red 40 (CI 16035).

PACKAGE FRONT AND BACK LABELS

m7.jpg